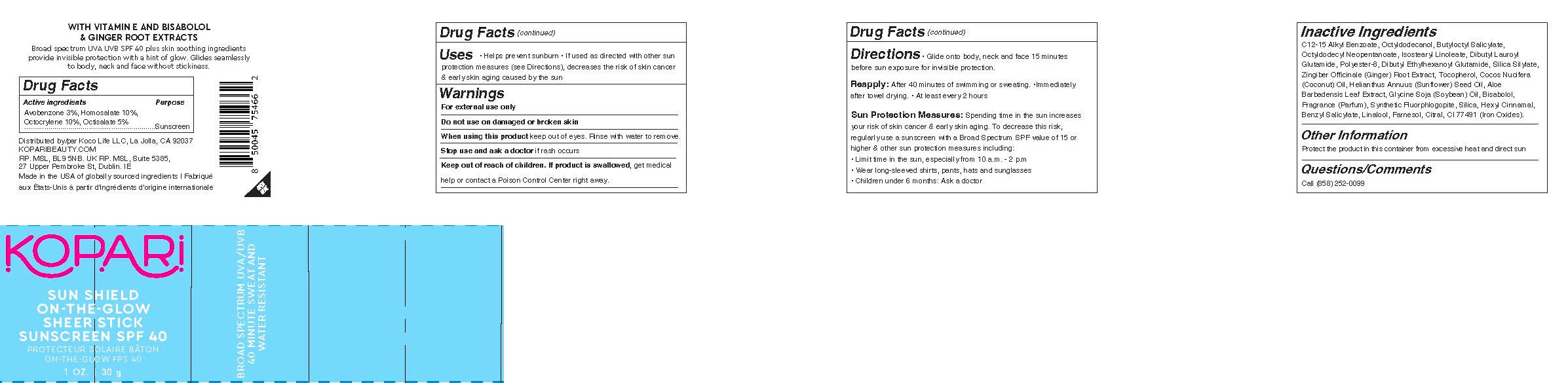 DRUG LABEL: Sun Shield On-the-Glow Sheer Stick SPF40
NDC: 84130-004 | Form: STICK
Manufacturer: Koco Life LLC
Category: otc | Type: HUMAN OTC DRUG LABEL
Date: 20240630

ACTIVE INGREDIENTS: OCTOCRYLENE 10 g/100 g; OCTISALATE 5 g/100 g; AVOBENZONE 3 g/100 g; HOMOSALATE 10 g/100 g
INACTIVE INGREDIENTS: DIBUTYL LAUROYL GLUTAMIDE; LEVOMENOL; LINALOOL, (+)-; ALKYL (C12-15) BENZOATE; OCTYLDODECANOL; BUTYLOCTYL SALICYLATE; SUNFLOWER OIL; ALOE VERA LEAF; CITRAL; OCTYLDODECYL NEOPENTANOATE; GINGER; FERRIC OXIDE RED; ISOSTEARYL LINOLEATE; SOYBEAN OIL; TOCOPHEROL; COCONUT OIL; MAGNESIUM POTASSIUM ALUMINOSILICATE FLUORIDE; SILICON DIOXIDE; .ALPHA.-HEXYLCINNAMALDEHYDE; FARNESOL; POLYESTER-8 (1400 MW, CYANODIPHENYLPROPENOYL CAPPED); DIBUTYL ETHYLHEXANOYL GLUTAMIDE; BENZYL SALICYLATE

Sun Shield On-the-Glow Sheer Stick SPF40

Active ingredients

Avobenzone 3%, Homosalate 10%, Octocrylene 10%, Octisalate 5%

Purpose

Avobenzone 3%, Homosalate 10%, Octocrylene 10%, Octisalate 5%...................Sunscreen

Uses

• Helps prevent sunburn • If used as directed with other sun protection measures (see Directions), decreases the risk of skin cancer & early skin aging caused by the sun

Warnings

For external use only

Do not use on damaged or broken skin

When using this product keep out of eyes. Rinse with water to remove.

Stop use and ask a doctor if rash occurs

Keep out of reach of children. If product is swallowed, get medical help or contact a Poison Control Center right away.

Directions

• Glide onto body, neck and face 15 minutesbefore sun exposure for invisible protection.

Reapply: After 40 minutes of swimming or sweating. •Immediately after towel drying. • At least every 2 hours

Sun Protection Measures: Spending time in the sun increases your risk of skin cancer & early skin aging. To decrease this risk, regularly use a sunscreen with a Broad Spectrum SPF value of 15 or higher & other sun protection measures including:• Limit time in the sun, especially from 10 a.m. - 2 p.m• Wear long-sleeved shirts, pants, hats and sunglasses• Children under 6 months: Ask a doctor

Inactive ingredients

C12-15 Alkyl Benzoate, Octyldodecanol, Butyloctyl Salicylate, Octyldodecyl Neopentanoate, Isostearyl Linoleate, Dibutyl Lauroyl Glutamide, Polyester-8, Dibutyl Ethylhexanoyl Glutamide, Silica Silylate, Zingiber Officinale (Ginger) Root Extract, Tocopherol, Cocos Nucifera (Coconut) Oil, Helianthus Annuus (Sunflower) Seed Oil, Aloe Barbadensis Leaf Extract, Glycine Soja (Soybean) Oil, Bisabolol, Fragrance (Parfum), Synthetic Fluorphlogopite, Silica, Hexyl Cinnamal, Benzyl Salicylate, Linalool, Farnesol, Citral, CI 77491 (Iron Oxides)

Other information

Protect the product in this container from excessive heat and direct sun

Questions/Comments

Call (858) 252-0099

PACKAGE LABEL

Kopari

Sun Shield

On-the-Glow

Sheer Stick

Sunscreen SPF 40

1 oz | 30 g